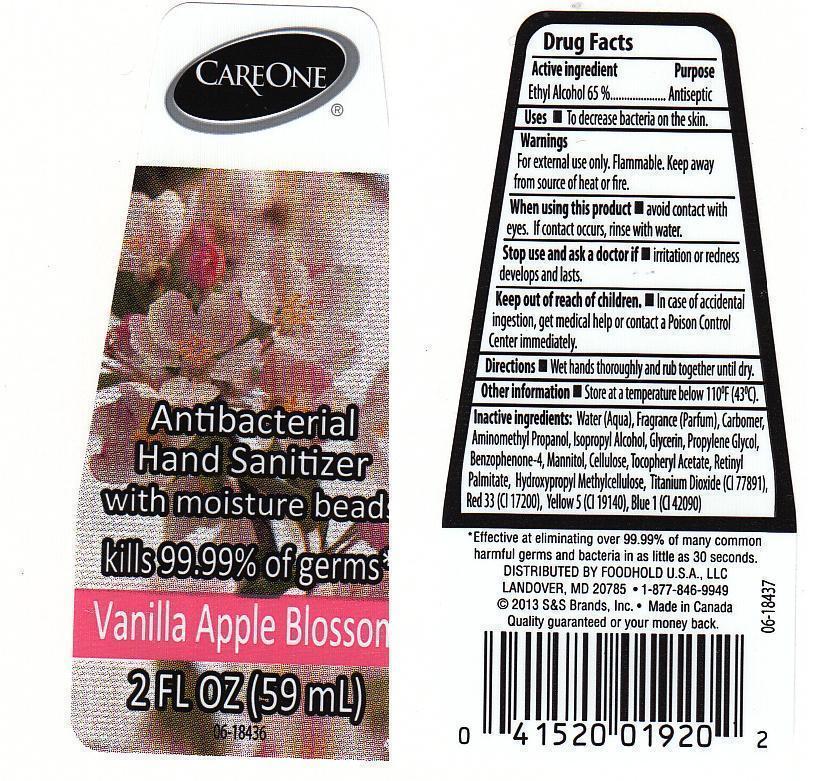 DRUG LABEL: CARE ONE
NDC: 41520-476 | Form: LIQUID
Manufacturer: AMERICAN SALES COMPANY
Category: otc | Type: HUMAN OTC DRUG LABEL
Date: 20130214

ACTIVE INGREDIENTS: ALCOHOL 650 mg/1 mL
INACTIVE INGREDIENTS: WATER; CARBOMER 934; AMINOMETHYLPROPANOL; ISOPROPYL ALCOHOL; GLYCERIN; PROPYLENE GLYCOL; SULISOBENZONE; MANNITOL; POWDERED CELLULOSE; .ALPHA.-TOCOPHEROL ACETATE; VITAMIN A PALMITATE; HYPROMELLOSES; TITANIUM DIOXIDE; D&C RED NO. 33; FD&C YELLOW NO. 5; FD&C BLUE NO. 1

DRUG FACTS

ACTIVE INGREDIENT

ETHYL ALCOHOL 65%

PURPOSE

ANTISEPTIC

USES

TO DECREASE BACTERIA ON THE SKIN.

WARNINGS

FOR EXTERNAL USE ONLY. FLAMMABLE. KEEP AWAY FOM SOURCE OF HEAT OR FIRE.

WHEN USING THIS PRODUCT

AVOID CONTACT WITH EYES. IF CONTACT OCCURS, RINSE WITH WATER.

STOP USING THIS PRODUCT AND ASK DOCTOR IF

IRRITATION OR REDNESS DEVELOPS AND LASTS.

KEEP OUT OF REACH OF CHILDREN.

IN CASE OF ACCIDENTAL INGESTION, GET MEDICAL HELP OR CONTACT A POISON CONTROL CENTER IMMEDIATELY.

DIRECTIONS

WET HANDS THOROUGHLY AND RUB TOGETHER UNTIL DRY.

OTHER INFORMATION

STORE AT A TEMPERATURE BELOW 110F (43C).

INACTIVE INGREDIENTS:

WATER (AQUA), FRAGRANCE (PARFUM), CARBOMER, AMINOMETHYL PROPANOL, ISOPROPYL ALCOHOL, GLYCERIN, PROPYLENE GLYCOL, BENZOPHENONE-4, MANNITOL, CELLULOSE, TOCOPHERYL ACETATE, RETINYL PALMITATE, HYDROXYPROPYL METHYLCELLULOSE, TITANIUM DIOXIDE (CI 77891), RED 33 (CI 17200), YELLOW 5 (CI 19140), BLUE 1 (CI 42090).